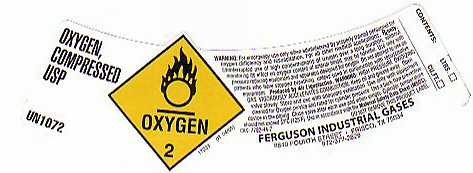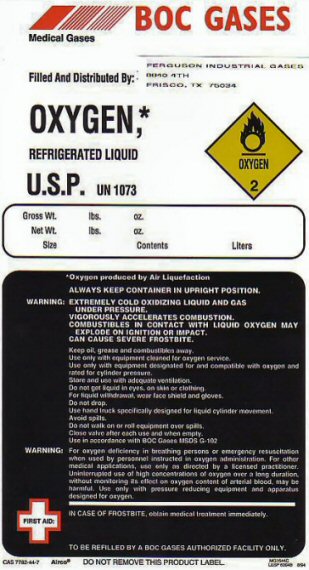 DRUG LABEL: OXYGEN
NDC: 63385-001 | Form: GAS
Manufacturer: Ferguson Industrial Gases dba Ferguson Enterprises
Category: prescription | Type: HUMAN PRESCRIPTION DRUG LABEL
Date: 20100101

ACTIVE INGREDIENTS: OXYGEN 99 L/100 L

OXYGEN COMPRESSED LABEL

OXYGEN COMPRESSED USP UN 1072 OXYGEN-2 PRODUCED BY AIR LIQUEFACTION. WARNING: HIGH PRESSURE OXIDIZING GAS. VIGOROUSLY ACCELERATES COMBUSTION. KEEP OIL AND GREASE AWAY. OPEN VALVE SLOWLY. STORE AND USE WITH ADEQUATE VENTILATION. USE ONLY WITH EQUIPMENT CLEANED FOR OXYGEN SERVICE AND RATED FOR CYLINDER PRESSURE. USE A BACK FLOW PREVENTATIVE DEVICE IN THE PIPING. CLOSE VALVE AFTER EACH USE AND WHEN EMPTY. CYLINDER TEMPERATURE SHOULD NOT EXCEED 52 C (125 F) USE IN ACCORDANCE WITH THE MATERIAL SAFETY DATA SHEET (MSDS) CAS: 7782-44-7 17033 (R 04/05)

CONTENTS________ LITERS_ CU FT_

REFRIGERATED LIQUID LABEL

OXYGEN REFRIGERATED LIQUID U.S.P. UN 1073 OXYGEN-2

GROSS WT________LBS OZ NET WT ___________ LBS OZ SIZE _______ CONTENTS_____LITERS

OXYGEN PRODUCED BY AIR LIQUEFACTION ALWAYS KEEP CONTAINER IN UPRIGHT POSITION.

WARNING: EXTREMELY COLD OXIDIZING LIQUID AND GAS UNDER PRESSURE. VIGOROUSLY ACCELERATES COMBUSTION. COMBUSTIBLES IN CONTACT WITH LIQUID OXYGEN MAY EXPLODE ON IGNITION OR IMPACT. CAN CAUSE SEVERE FROSTBITE.

KEEP OIL GREASE AND COMBUSTIBLES AWAY. USE ONLY WITH EQUIPMENT CLEANED FOR OXYGEN SERVICE. USE ONLY WITH EQUIPMENT DESIGNATED FOR AND COMPATIBLE WITH OXYGEN AND RATED FOR CYLINDER PRESSURE. STORE AND USE WITH ADEQUATE VENTILATION. DO NOT GET LIQUID IN EYES, ON SKIN OR CLOTHING. FOR LIQUID WITHDRAWAL WEAR FACE SHIELD AND GLOVES. DO NOT DROP. USE HAND TRUCK SPECIFICALLY DESIGNED FOR LIQUID CYLINDER MOVEMENT. AVOID SPILLS. DO NOT WALK ON OR ROLL EQUIPMENT OVER SPILLS. CLOSE VALVE AFTER EACH USE AND WHEN EMPTY. USE IN ACCORDANCE WITH BOC GASES MSDS G-102

IN CASE OF FROSTBITE OBTAIN MEDICAL TREATMENT IMMEDIATELY.

TO BE REFILLED BY A BOC GASES AUTHORIZED FACILITY ONLY DO NOT REMOVE THIS PRODUCT LABEL.

CAS 7782-44-7 8/94

PRODUCT WARNINGS AND PRECAUTIONS

WARNING: FOR EMERGENCY USE ONLY WHEN ADMINISTERED BY PROPERLY TRAINED PERSONNEL FOR OXYGEN DEFICIENCY AND RESUSCITATION. FOR ALL OTHER MEDICAL APPLICATIONS Rx ONLY. UNINTERRUPTED USE OF HIGH CONCENTRATIONS OF OXYGEN OVER A LONG DURATION WITHOUT MONITORING ITS AFFECT ON OXYGEN CONTENT OF ARTERIAL BLOOD MAY BE HARMFUL. USE ONLY WITH PRESSURE REDUCING EQUIPMENT AND APPARATUS DESIGNED FOR OXYGEN. DO NOT ATTEMPT TO USE ON PATIENTS WHO HAVE STOPPED BREATHING UNLESS USED IN CONJUNCTION WITH RESUSCITATIVE EQUIPMENT.